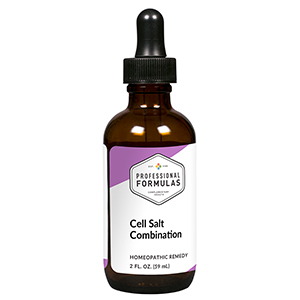 DRUG LABEL: Cell Salt Combination
NDC: 63083-8013 | Form: LIQUID
Manufacturer: Professional Complementary Health Formulas
Category: homeopathic | Type: HUMAN OTC DRUG LABEL
Date: 20190815

ACTIVE INGREDIENTS: ANHYDROUS DIBASIC CALCIUM PHOSPHATE 6 [hp_X]/59 mL; POTASSIUM CHLORIDE 6 [hp_X]/59 mL; CALCIUM SULFATE ANHYDROUS 6 [hp_X]/59 mL; FERROSOFERRIC PHOSPHATE 6 [hp_X]/59 mL; CALCIUM FLUORIDE 6 [hp_X]/59 mL; POTASSIUM PHOSPHATE, UNSPECIFIED FORM 6 [hp_X]/59 mL; SODIUM CHLORIDE 6 [hp_X]/59 mL; POTASSIUM SULFATE 6 [hp_X]/59 mL; MAGNESIUM PHOSPHATE, DIBASIC TRIHYDRATE 6 [hp_X]/59 mL; SODIUM PHOSPHATE, DIBASIC, HEPTAHYDRATE 6 [hp_X]/59 mL; SILICON DIOXIDE 6 [hp_X]/59 mL; SODIUM SULFATE 6 [hp_X]/59 mL
INACTIVE INGREDIENTS: ALCOHOL; WATER

CSMX

ACTIVE INGREDIENTS

Calcarea phosphorica 6X, 12X, 30X
Kali muriaticum 6X, 12X, 30X
Calcarea sulphurica 6X, 12X, 30X
Ferrum phosphoricum 6X, 12X, 30X
Calcarea fluorica 6X, 12X, 30X
Kali phosphoricum 6X, 12X, 30X
Natrum muriaticum 6X, 12X, 30X
Kali sulphuricum 6X, 12X, 30X
Magnesia phosphorica 6X, 12X, 30X
Natrum phosphoricum 6X, 12X, 30X
Silicea 6X, 12X, 30X
Natrum sulphuricum 6X , 12X, 30X

QUESTIONS

Professional Formulas

PO Box 2034 Lake Oswego, OR 97035

INDICATIONS

Use according to standard homeopathic indications for self-limiting conditions. Common Materia Medica indications: colds, headaches, exhaustion, minor aches and pains.*

PURPOSE

*Claims based on traditional homeopathic practice, not accepted medical evidence. Not FDA evaluated.

WARNINGS

In case of overdose, get medical help or contact a poison control center right away.

Keep out of the reach of children.

PREGNANCY OR BREAST FEEDING

If pregnant or breastfeeding, ask a healthcare professional before use.

DIRECTIONS

Place drops under tongue 30 minutes before/after meals. Adults and children 12 years and over: Take 10 drops up to 3 times per day. Consult a physician for use in children under 12 years of age.

OTHER INFORMATION

Tamper resistant. If seal is broken, do not use. After opening, close container tightly and store at room temperature away from heat.

INACTIVE INGREDIENTS

20% ethanol, purified water.

LABEL

Est 1985

Professional Formulas

Complementary Health

Cell Salt Combination

Homeopathic Remedy

2 FL. OZ. (59 mL)